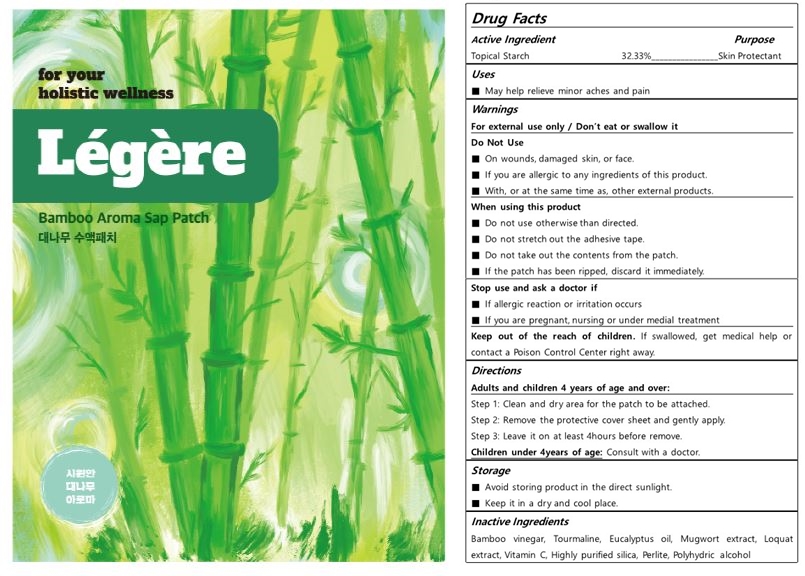 DRUG LABEL: Legere Bamboo Foot Patch
NDC: 82504-102 | Form: PATCH
Manufacturer: Myriad Co., Ltd.
Category: otc | Type: HUMAN OTC DRUG LABEL
Date: 20221229

ACTIVE INGREDIENTS: STARCH, CORN 32.33 g/100 g
INACTIVE INGREDIENTS: SILICON DIOXIDE; PHYLLOSTACHYS EDULIS VINEGAR; PERLITE; ASCORBIC ACID; EUCALYPTUS OIL; POLIGLUSAM; ARTEMISIA PRINCEPS LEAF; ERIOBOTRYA JAPONICA LEAF; GLYCERYL CAPRYLATE; SCHORL TOURMALINE; SORBITOL; ETHYLHEXYLGLYCERIN

Légère bamboo

PURPOSE

Skin Protectant

Uses

May help relieve minor aches and pain

Active Ingredient

Topical Starch 32.33%

Warnings

For external use only / Don’t eat or swallow it

Warnings

Keep out of the reach of children.

If swallowed, get medical help or contact a Poison Control Center right away.

When using this product

■ Do not use otherwise than directed.

■ Do not stretch out the adhesive tape.

■ Do not take out the contents from the patch.

■ If the patch has been ripped, discard it immediately.

Stop use and ask a doctor if

■ If allergic reaction or irritation occurs

■ If you are pregnant, nursing or under medial treatment

Warnings

■ On wounds, damaged skin, or face.

■ If you are allergic to any ingredients of this product.

■ With, or at the same time as, other external products.

Inactive Ingredients

Bamboo vinegar, Tourmaline, Eucalyptus oil, Mugwort extract, Loquat extract, Vitamin C, Highly purified silica, Perlite, Polyhydric alcohol

directions

Adults and children 4 years of age and over:

Step 1: Clean and dry area for the patch to be attached.

Step 2: Remove the protective cover sheet and gently apply.

Step 3: Leave it on at least 4hours before remove.

Children under 4years of age: Consult with a doctor.

Légère Bamboo Foot Patch

82504-102-01